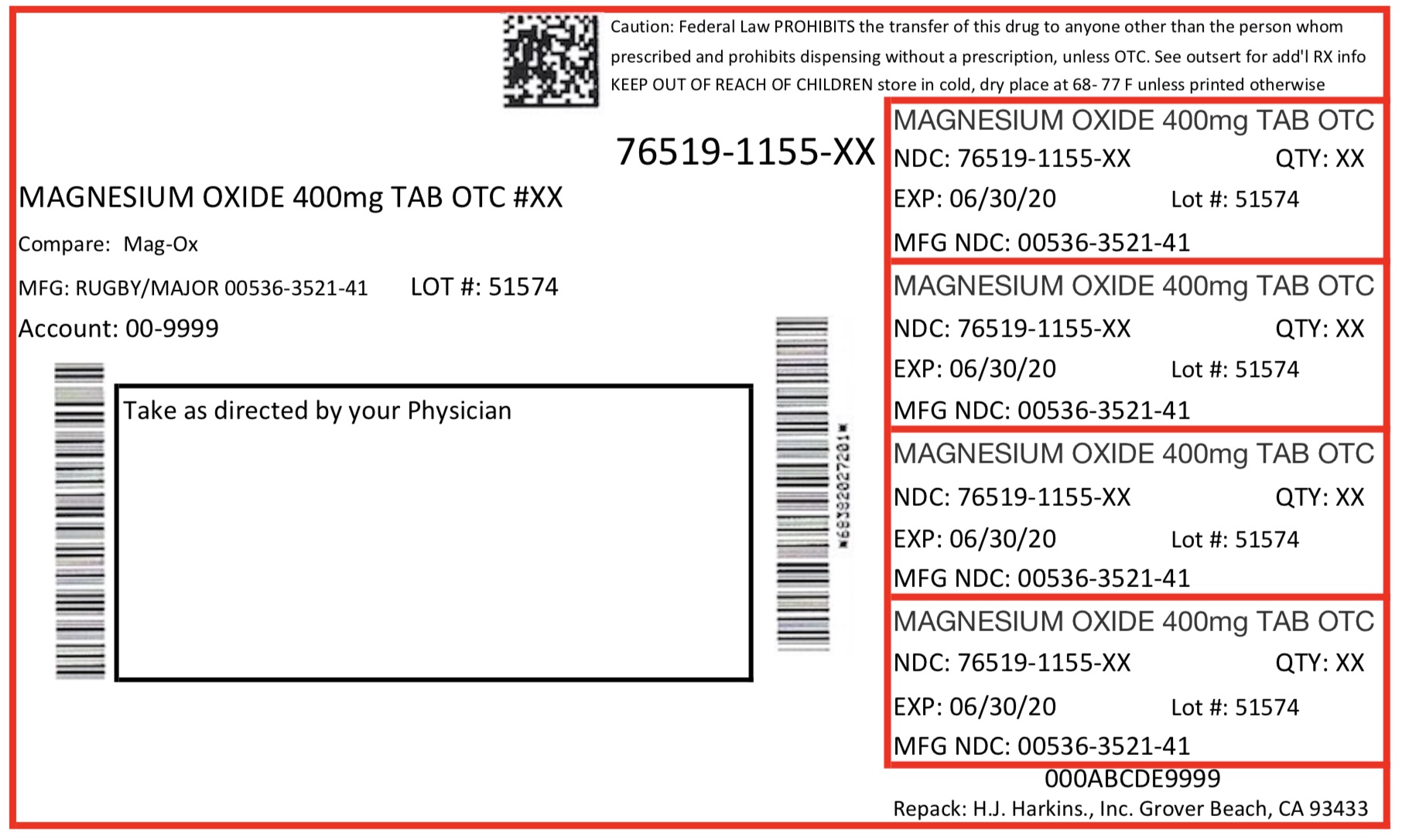 DRUG LABEL: MAGNESIUM OXIDE
NDC: 76519-1155 | Form: TABLET
Manufacturer: H. J. Harkins Company Inc.
Category: otc | Type: HUMAN OTC DRUG LABEL
Date: 20171219

ACTIVE INGREDIENTS: MAGNESIUM OXIDE 400 mg/1 1
INACTIVE INGREDIENTS: CROSCARMELLOSE SODIUM; CELLULOSE, MICROCRYSTALLINE; STEARIC ACID; SILICON DIOXIDE

Active Ingredient

Magnesium Oxide 400 mg (241.3 mg Elemental Magnesium)

Purpose

relieves:

acid indigestion
upset stomach

KEEP OUT OF REACH OF CHILDREN

Ask a doctor before use if

you have kidney disease
you are taking a prescription drug (antacids may interact with certain prescription drugs)
you are pregnant or breast feeding.

Do not take more than 2 tablets in a 24 hour period.

May have a laxative effect.

Keep out of reach of children.

Dosage and Administration

take one or two antacid tablets daily. Do not exceed two tablets unless directed by a physician.

Storage & Handling

Store at controlled room temperature 15° to 30°C (59° to 86°F).
Tamper evident, do not use if imprinted safety seal under cap is broken or missing.

Inactive Ingredients

Croscarmellose Sodium, Microcrystalline Cellulose, Silicon Dioxide, and Stearic Acid.

Indications & Usage

Antacid

Warnings

Do not take this product if you are presently taking a prescription drug without consulting your physician or other health care professional. If you have kidney disease, take only under the supervision of a physician. May have a laxative effect. If pregnant or breast-feeding, ask a health professional before use.

Pregnancy or Breast Feeding

If pregnant or breast-feeding, ask a health professional before use.

Keep Out of Reach of Children